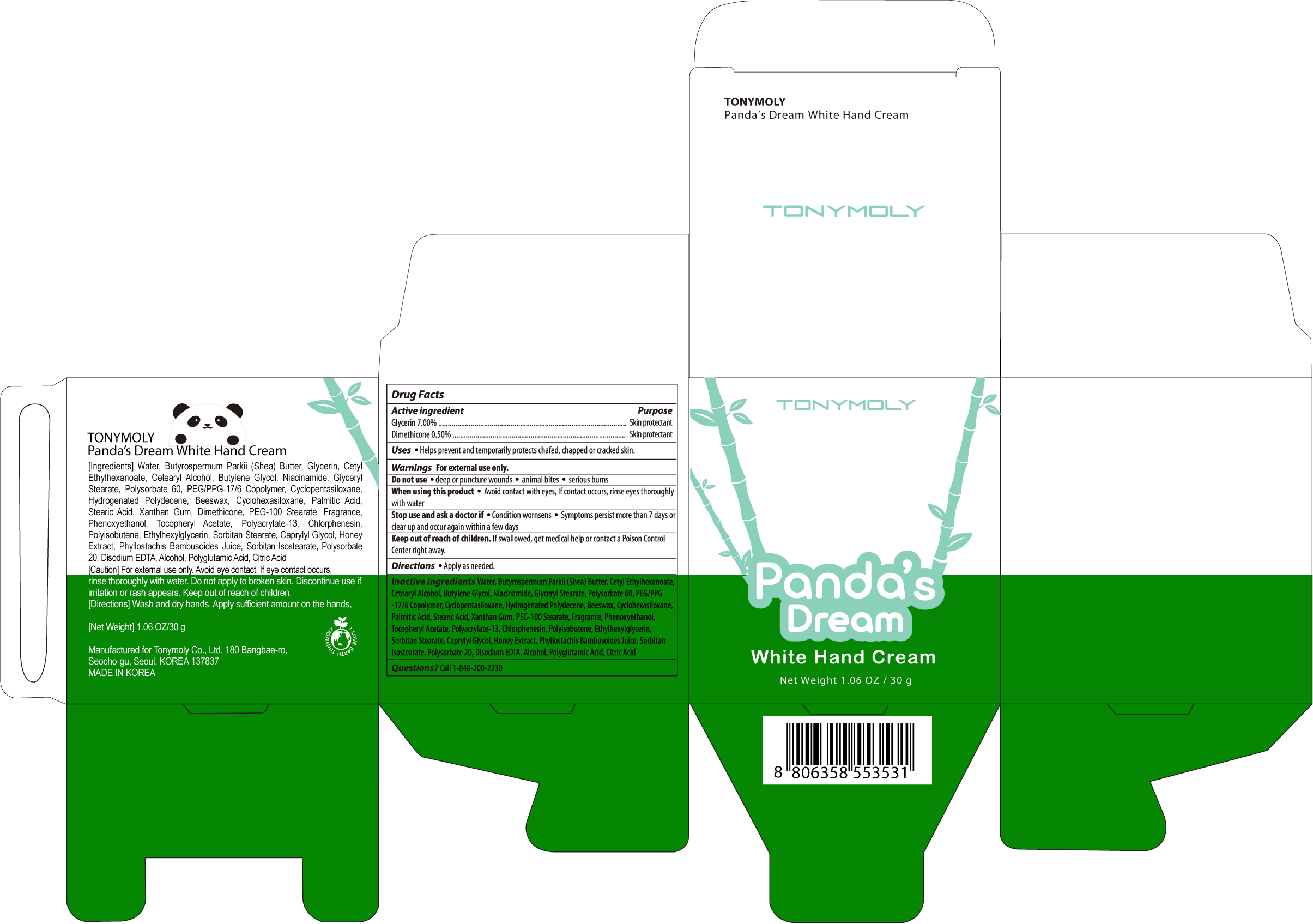 DRUG LABEL: TONYMOLY Pandas Dream White Hand Cream
NDC: 59078-152 | Form: CREAM
Manufacturer: Tonymoly Co., Ltd.
Category: otc | Type: HUMAN OTC DRUG LABEL
Date: 20160211

ACTIVE INGREDIENTS: DIMETHICONE 0.15 g/30 g; GLYCERIN 2.1 g/30 g
INACTIVE INGREDIENTS: CETOSTEARYL ALCOHOL; NIACINAMIDE; SHEA BUTTER; BUTYLENE GLYCOL; GLYCERYL MONOSTEARATE; CYCLOMETHICONE 5; PALMITIC ACID; PEG-100 STEARATE; CYCLOMETHICONE 6; YELLOW WAX; XANTHAN GUM; PHENOXYETHANOL; .ALPHA.-TOCOPHEROL ACETATE; CHLORPHENESIN; ETHYLHEXYLGLYCERIN; SORBITAN MONOSTEARATE; CAPRYLYL GLYCOL; HONEY; POLYSORBATE 20; EDETATE DISODIUM; POLYGALIC ACID; CITRIC ACID MONOHYDRATE; WATER; CETYL ETHYLHEXANOATE; POLYSORBATE 60; STEARIC ACID; SORBITAN ISOSTEARATE; ALCOHOL; PEG/PPG-17/6 COPOLYMER

Active Ingredients

Glycerin 7.00%, Dimethicone 0.50%

Purpose

Skin Protectant

Uses

Helps prevent and temporarily protects chafed, chapped or cracked skin.

Warnings

For external use only.

Do not use

- deep or puncture wounds
- animal bites
- serious burns

Stop use and ask a doctor if

- Condition wornsens
- Symptoms persist more than 7 days or clear up and occur again within a few days

When using this product

- Avoid contact with eyes, If contact occurs, rinse eyes thoroughly with water

Keep out of reach of children

If swallowed, get medical help or contact a Poison Control Center right away.

Directions

Apply as needed.

Inactive Ingredients

Water, Butyrospermum Parkii (Shea) Butter, Cetyl Ethylhexanoate, Cetearyl Alcohol, Butylene Glycol, Niacinamide, Glyceryl Stearate, Polysorbate 60, PEG/PPG-17/6 Copolymer, Cyclopentasiloxane, Hydrogenated Polydecene, Beeswax, Cyclohexasiloxane, Palmitic Acid, Stearic Acid, Xanthan Gum, PEG-100 Stearate, Fragrance, Phenoxyethanol, Tocopheryl Acetate, Polyacrylate-13, Chlorphenesin, Polyisobutene, Ethylhexylglycerin, Sorbitan Stearate, Caprylyl Glycol, Honey Extract, Phyllostachis Bambusoides Juice, Sorbitan Isostearate, Polysorbate 20, Disodium EDTA, Alcohol, Polyglutamic Acid, Citric Acid

Questions?

Call 1-848-200-2230